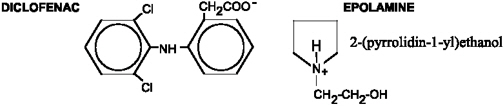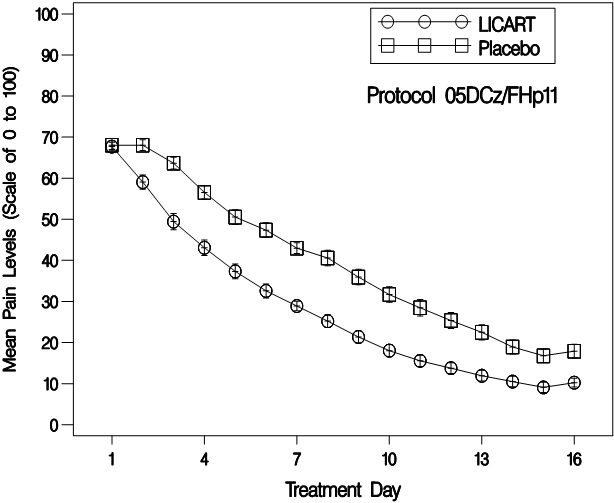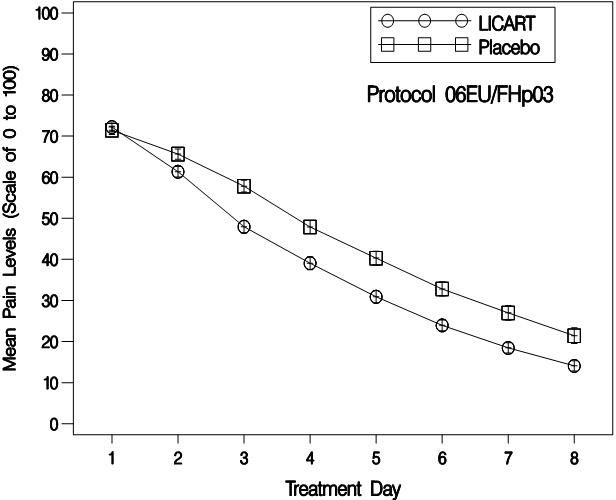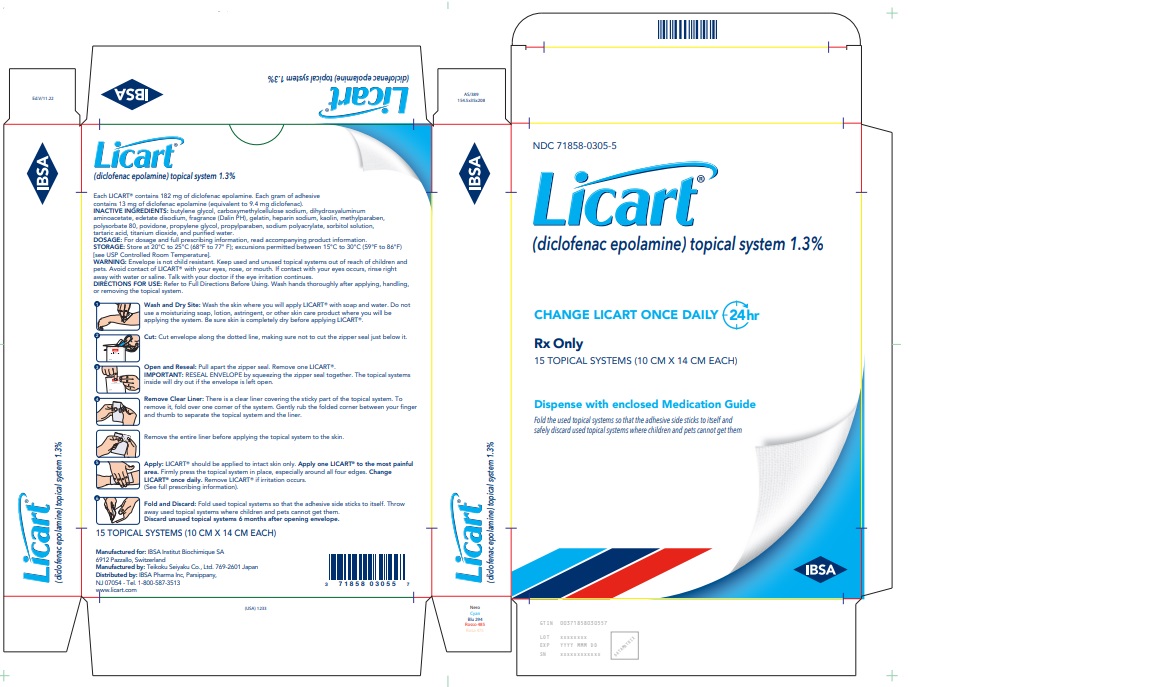 DRUG LABEL: LICART
NDC: 71858-0305 | Form: SYSTEM
Manufacturer: IBSA Pharma Inc.
Category: prescription | Type: HUMAN PRESCRIPTION DRUG LABEL
Date: 20260105

ACTIVE INGREDIENTS: DICLOFENAC EPOLAMINE 0.013 g/1 1
INACTIVE INGREDIENTS: CARBOXYMETHYLCELLULOSE SODIUM, UNSPECIFIED; DIHYDROXYALUMINUM AMINOACETATE; EDETATE DISODIUM; GELATIN, UNSPECIFIED; HEPARIN SODIUM; KAOLIN; METHYLPARABEN; POLYSORBATE 80; POVIDONE, UNSPECIFIED; PROPYLENE GLYCOL; PROPYLPARABEN; SORBITOL; TARTARIC ACID; TITANIUM DIOXIDE; WATER; BUTYLENE GLYCOL

HIGHLIGHTS OF PRESCRIBING INFORMATION

These highlights do not include all the information needed to use LICART® safely and effectively. See full prescribing information for LICART.
LICART® (diclofenac epolamine) topical system
Initial U.S. Approval: 1988

WARNING: RISK OF SERIOUS CARDIOVASCULAR and GASTROINTESTINAL EVENTS

See full prescribing information for complete boxed warning.

- Nonsteroidal anti-inflammatory drugs (NSAIDs) cause an increased risk of serious cardiovascular thrombotic events, including myocardial infarction and stroke, which can be fatal. This risk may occur early in the treatment and may increase with duration of use (5.1)
- LICART is contraindicated in the setting of coronary artery bypass graft (CABG) surgery. (4, 5.1)
- NSAIDs cause an increased risk of serious gastrointestinal (GI) adverse events including bleeding, ulceration, and perforation of the stomach or intestines, which can be fatal. These events can occur at any time during use and without warning symptoms. Elderly patients and patients with a prior history of peptic ulcer disease and/or GI bleeding are at greater risk for serious GI events. (5.2)

RECENT MAJOR CHANGES

Warning and Precautions (5.9) | 11/2024

1 INDICATIONS AND USAGE

LICART contains diclofenac epolamine, which is a nonsteroidal anti-inflammatory drug (NSAID), and is indicated for the topical treatment of acute pain due to minor strains, sprains, and contusions (1)

2 DOSAGE AND ADMINISTRATION

- Use the lowest effective dose for shortest duration consistent with individual patient treatment goals (2.1)
- See the Full Prescribing Information for important administration instructions (2.1)
- Do not apply to damaged or non-intact skin (2.1)
- The recommended dose is one (1) LICART to the most painful area once daily (2.2)

3 DOSAGE FORM AND STRENGTHS

- LICART (diclofenac epolamine) topical system 1.3% for topical use. Each individual LICART is debossed. (3)

4 CONTRAINDICATIONS

- Known hypersensitivity to diclofenac or any components of the drug product (4)
- History of asthma, urticaria, or allergic-type reactions after taking aspirin or other NSAIDs (4)
- In the setting of CABG surgery (4)
- For use on non-intact or damaged skin (4)

5 WARNINGS AND PRECAUTIONS

- Hepatotoxicity: Inform patients of warning signs and symptoms of hepatotoxicity. Discontinue if abnormal liver tests persist or worsen or if clinical signs and symptoms of liver disease develop (5.3)
- Hypertension: Patients taking some antihypertensive medications may have impaired response to these therapies when taking NSAIDs. Monitor blood pressure (5.4, 7)
- Heart Failure and Edema: Avoid use of LICART in patients with severe heart failure unless benefits are expected to outweigh risk of worsening heart failure (5.5)
- Renal Toxicity: Monitor renal function in patients with renal or hepatic impairment, heart failure, dehydration, or hypovolemia. Avoid use of LICART in patients with advanced renal disease unless benefits are expected to outweigh risk of worsening renal function (5.6)
- Anaphylactic Reactions: Seek emergency help if an anaphylactic reaction occurs (5.7)
- Exacerbation of Asthma Related to Aspirin Sensitivity: LICART is contraindicated in patients with aspirin-sensitive asthma. Monitor patients with preexisting asthma (without aspirin sensitivity) (5.8)
- Serious Skin Reactions: Discontinue LICART at first appearance of skin rash or other signs of hypersensitivity (5.9)
- Drug Reaction with Eosinophilia and Systemic Symptoms (DRESS): Discontinue and evaluate clinically (5.10).
- Fetal Toxicity: Limit use of NSAIDs, including LICART, between about 20 to 30 weeks in pregnancy due to the risk of oligohydramnios/fetal renal dysfunction. Avoid use of NSAIDs in women at about 30 weeks gestation and later in pregnancy due to the risks of oligohydramnios/fetal renal dysfunction and premature closure of the fetal ductus arteriosus (5.11, 8.1)
- Hematologic Toxicity: Monitor hemoglobin or hematocrit in patients with any signs or symptoms of anemia (5.12, 7)

6 ADVERSE REACTIONS

Most common adverse reactions for LICART are application site pruritus and other application site reactions (6.1)

To report SUSPECTED ADVERSE REACTIONS, contact IBSA Pharma Inc. at 1-800-587-3513 or FDA at 1-800-FDA-1088 or www.fda.gov/medwatch.

7 DRUG INTERACTIONS

- Drugs that Interfere with Hemostasis (e.g.; warfarin, aspirin, SSRIs/SNRIs): Monitor patients for bleeding who are concomitantly using LICART with drugs that interfere with hemostasis. Concomitant use of LICART and analgesic doses of aspirin is not generally recommended (7)
- ACE Inhibitors, Angiotensin Receptor Blockers (ARB), or Beta-Blockers: Concomitant use with LICART may diminish the antihypertensive effect of these drugs. Monitor blood pressure (7)
- ACE Inhibitors and ARBs: Concomitant use with LICART in elderly, volume depleted, or those with renal impairment may result in deterioration of renal function. In such high-risk patients, monitor for signs of worsening renal function (7)
- Diuretics: NSAIDs can reduce natriuretic effect of furosemide and thiazide diuretics. Monitor patients to assure diuretic efficacy including antihypertensive effects (7)
- Digoxin: Concomitant use with LICART may increase serum concentration and prolong half-life of digoxin. Monitor serum digoxin levels (7)

8 USE IN SPECIFIC POPULATIONS

- Infertility: NSAIDs are associated with reversible infertility. Consider withdrawal of LICART in women who have difficulties conceiving (8.3)

FULL PRESCRIBING INFORMATION

WARNING: RISK OF SERIOUS CARDIOVASCULAR and GASTROINTESTINAL EVENTS

Cardiovascular Thrombotic Events

- Nonsteroidal anti-inflammatory drugs (NSAIDs) cause an increased risk of serious cardiovascular thrombotic events, including myocardial infarction and stroke, which can be fatal. This risk may occur early in treatment and may increase with duration of use [See Warnings and Precautions (5.1)] .
- LICART is contraindicated in the setting of coronary artery bypass graft (CABG) surgery [See Contraindications (4) and Warnings and Precautions (5.1)].

Gastrointestinal Bleeding, Ulceration, and Perforation

- NSAIDs cause an increased risk of serious gastrointestinal (GI) adverse events including bleeding, ulceration, and perforation of the stomach or intestines, which can be fatal. These events can occur at any time during use and without warning symptoms. Elderly patients and patients with a prior history of peptic ulcer disease and/or GI bleeding are at greater risk for serious GI events [See Warnings and Precautions (5.2)] .

1 INDICATIONS AND USAGE

LICART is indicated for the topical treatment of acute pain due to minor strains, sprains, and contusions.

2 DOSAGE AND ADMINISTRATION

2.1 Important Dosage and Administration Information

Use the lowest effective dosage for the shortest duration consistent with individual patient treatment goals [see Warnings and Precautions (5)] .

LICART is intended for topical use only.

Convey the following important administration instructions to the patient:

- If LICART begins to peel-off, the edges of the topical system may be taped down. If problems with adhesion persist, patients may overlay the topical system with a mesh netting sleeve, where appropriate (e.g., to secure topical systems applied to ankles, knees, or elbows). The mesh netting sleeve (e.g., Curad® Hold Tite™, Surgilast® Tubular Elastic Dressing) must allow air to pass through and not be occlusive (i.e., non-breathable) [Curad ® Hold Tite™ is a trademark of Medline Industries, Inc., and Surgilast ® Tubular Elastic Dressing is a trademark of Derma Sciences, Inc.] .
- Do not apply LICART to non-intact or damaged skin resulting from any etiology, e.g., exudative dermatitis, eczema, infected lesion, burns or wounds.
- Do not wear a LICART topical system when bathing or showering.
- Wash your hands after applying, handling, or removing the topical system.
- Avoid contact with eyes.
- Do not use LICART in combination with an oral NSAID unless the benefit outweighs the risk and periodic laboratory evaluations are conducted.

2.2 Recommended Dose

The recommended dose is one (1) LICART topical system to the most painful area once daily.

3 DOSAGE FORM AND STRENGTHS

Topical System: 1.3% diclofenac epolamine (10 cm × 14 cm) debossed with "LICART (diclofenac epolamine) topical system 1.3%".

4 CONTRAINDICATIONS

LICART is contraindicated in the following patients:

- Known hypersensitivity (e.g., anaphylactic reactions and serious skin reactions) to diclofenac or any components of the drug product [see Warnings and Precautions (5.7, 5.9)].
- History of asthma, urticaria, or other allergic-type reactions after taking aspirin or other NSAIDs. Severe, sometimes fatal, anaphylactic reactions to NSAIDs have been reported in such patients [see Warnings and Precautions (5.7, 5.8)].
- In the setting of coronary artery bypass graft (CABG) surgery [see Warnings and Precautions (5.1)].
- On non-intact or damaged skin resulting from any etiology, including exudative dermatitis, eczema, infected lesions, burns or wounds.

5 WARNINGS AND PRECAUTIONS

5.1 Cardiovascular Thrombotic Events

Clinical trials of several COX-2 selective and nonselective NSAIDs of up to three years duration have shown an increased risk of serious cardiovascular (CV) thrombotic events, including myocardial infarction (MI) and stroke, which can be fatal. Based on available data, it is unclear that the risk for CV thrombotic events is similar for all NSAIDs. The relative increase in serious CV thrombotic events over baseline conferred by NSAID use appears to be similar in those with and without known CV disease or risk factors for CV disease. However, patients with known CV disease or risk factors had a higher absolute incidence of excess serious CV thrombotic events, due to their increased baseline rate. Some observational studies found that this increased risk of serious CV thrombotic events began as early as the first weeks of treatment. The increase in CV thrombotic risk has been observed most consistently at higher doses.

To minimize the potential risk for an adverse CV event in NSAID-treated patients, use the lowest effective dose for the shortest duration possible. Physicians and patients should remain alert for the development of such events, throughout the entire treatment course, even in the absence of previous CV symptoms. Patients should be informed about the symptoms of serious CV events and the steps to take if they occur.

There is no consistent evidence that concurrent use of aspirin mitigates the increased risk of serious CV thrombotic events associated with NSAID use. The concurrent use of aspirin and an NSAID, such as diclofenac, increases the risk of serious gastrointestinal (GI) events [see Warnings and Precautions (5.2)].

Status Post Coronary Artery Bypass Graft (CABG) Surgery

Two large, controlled clinical trials of a COX-2 selective NSAID for the treatment of pain in the first 10–14 days following CABG surgery found an increased incidence of myocardial infarction and stroke. NSAIDs are contraindicated in the setting of CABG [see Contraindications (4)] .

Post-MI Patients

Observational studies conducted in the Danish National Registry have demonstrated that patients treated with NSAIDs in the post-MI period were at increased risk of reinfarction, CV-related death, and all-cause mortality beginning in the first week of treatment. In this same cohort, the incidence of death in the first year post-MI was 20 per 100 person years in NSAID-treated patients compared to 12 per 100 person years in non-NSAID exposed patients. Although the absolute rate of death declined somewhat after the first year post-MI, the increased relative risk of death in NSAID users persisted over at least the next four years of follow-up.

Avoid the use of LICART in patients with a recent MI unless the benefits are expected to outweigh the risk of recurrent CV thrombotic events. If LICART is used in patients with a recent MI, monitor patients for signs of cardiac ischemia.

5.2 Gastrointestinal Bleeding, Ulceration and Perforation

NSAIDs, including diclofenac, cause serious gastrointestinal (GI) adverse events including inflammation, bleeding, ulceration, and perforation of the esophagus, stomach, small intestine, or large intestine, which can be fatal. These serious adverse events can occur at any time, with or without warning symptoms, in patients treated with NSAIDs.

Only one in five patients who develop a serious upper GI adverse event on NSAID therapy is symptomatic. Upper GI ulcers, gross bleeding, or perforation caused by NSAIDs occurred in approximately 1% of patients treated for 3-6 months, and in about 2% - 4% of patients treated for one year. However, even short-term NSAID therapy is not without risk.

Risk Factors for GI Bleeding, Ulceration, and Perforation

Patients with a prior history of peptic ulcer disease and/or GI bleeding who used NSAIDs had a greater than 10-fold increased risk for developing a GI bleed compared to patients without these risk factors. Other factors that increase the risk of GI bleeding in patients treated with NSAIDs include longer duration of NSAID therapy; concomitant use of oral corticosteroids, aspirin, anticoagulants, or selective serotonin reuptake inhibitors (SSRIs); smoking; use of alcohol; older age; and poor general health status. Most postmarketing reports of fatal GI events occurred in elderly or debilitated patients. Additionally, patients with advanced liver disease and/or coagulopathy are at increased risk for GI bleeding.

Strategies to Minimize the GI Risks in NSAID-Treated Patients:

- Use the lowest effective dosage for the shortest possible duration.
- Avoid administration of more than one NSAID at a time.
- Avoid use in patients at higher risk unless benefits are expected to outweigh the increased risk of bleeding. For such patients, as well as those with active GI bleeding, consider alternate therapies other than NSAIDs.
- Remain alert for signs and symptoms of GI ulceration and bleeding during NSAID therapy.
- If a serious GI adverse event is suspected, promptly initiate evaluation and treatment, and discontinue LICART until a serious GI adverse event is ruled out.
- In the setting of concomitant use of low-dose aspirin for cardiac prophylaxis, monitor patients more closely for evidence of GI bleeding [see Drug Interactions (7)] .

5.3 Hepatotoxicity

In clinical trials of oral diclofenac containing products, meaningful elevations (i.e., more than 3 times the ULN) of AST (SGOT) were observed in about 2% of approximately 5,700 patients at some time during diclofenac treatment (ALT was not measured in all studies).

In an open-label, controlled trial of 3,700 patients treated with oral diclofenac sodium for 2-6 months, patients were monitored first at 8 weeks and 1,200 patients were monitored again at 24 weeks. Meaningful elevations of ALT and/or AST occurred in about 4% of the 3,700 patients and included marked elevations (greater than 8 times the ULN) in about 1% of the 3,700 patients. In that open-label study, a higher incidence of borderline (less than 3 times the ULN), moderate (3-8 times the ULN), and marked (greater than 8 times the ULN) elevations of ALT or AST was observed in patients receiving diclofenac when compared to other NSAIDs. Elevations in transaminases were seen more frequently in patients with osteoarthritis than in those with rheumatoid arthritis.

Almost all meaningful elevations in transaminases were detected before patients became symptomatic. Abnormal tests occurred during the first 2 months of therapy with diclofenac in 42 of the 51 patients in all trials who developed marked transaminase elevations.

In post-marketing reports, cases of drug-induced hepatotoxicity have been reported in the first month, and in some cases, the first 2 months of therapy, but can occur at any time during treatment with diclofenac. Post-marketing surveillance has reported cases of severe hepatic reactions, including liver necrosis, jaundice, fulminant hepatitis with and without jaundice, and liver failure. Some of these reported cases resulted in fatalities or liver transplantation.

In a European retrospective population-based, case-controlled study, 10 cases of diclofenac associated drug-induced liver injury with current use compared with non-use of diclofenac were associated with a statistically significant 4-fold adjusted odds ratio of liver injury. In this particular study, based on an overall number of 10 cases of liver injury associated with diclofenac, the adjusted odds ratio increased further with female gender, doses of 150 mg or more, and duration of use for more than 90 days.

Physicians should measure transaminases at baseline and periodically in patients receiving long-term therapy with diclofenac, because severe hepatotoxicity may develop without a prodrome of distinguishing symptoms. The optimum times for making the first and subsequent transaminase measurements are not known. Based on clinical trial data and post-marketing experiences, transaminases should be monitored within 4 to 8 weeks after initiating treatment with diclofenac. However, severe hepatic reactions can occur at any time during treatment with diclofenac.

If abnormal liver tests persist or worsen, if clinical signs and/or symptoms consistent with liver disease develop, or if systemic manifestations occur (e.g., eosinophilia, rash, abdominal pain, diarrhea, dark urine, etc.), LICART should be discontinued immediately.

Inform patients of the warning signs and symptoms of hepatotoxicity (e.g., nausea, fatigue, lethargy, diarrhea, pruritus, jaundice, right upper quadrant tenderness, and "flu-like" symptoms). If clinical signs and symptoms consistent with liver disease develop, or if systemic manifestations occur (e.g., eosinophilia, rash, etc.), discontinue LICART immediately, and perform a clinical evaluation of the patient. To minimize the potential risk for an adverse liver related event in patients treated with LICART, use the lowest effective dose for the shortest duration possible. Exercise caution when prescribing LICART with concomitant drugs that are known to be potentially hepatotoxic (e.g., acetaminophen, antibiotics, anti-epileptics).

5.4 Hypertension

NSAIDs, including LICART, can lead to new onset or worsening of preexisting hypertension, either of which may contribute to the increased incidence of CV events. Patients taking angiotensin converting enzyme (ACE) inhibitors, thiazide diuretics, or loop diuretics may have impaired response to these therapies when taking NSAIDs [see Drug Interactions (7)] .

Monitor blood pressure (BP) during the initiation of NSAID treatment and throughout the course of therapy.

5.5 Heart Failure and Edema

The Coxib and traditional NSAID Trialists' Collaboration meta-analysis of randomized controlled trials demonstrated an approximately two-fold increase in hospitalizations for heart failure in COX-2 selective-treated patients and nonselective NSAID-treated patients compared to placebo-treated patients. In a Danish National Registry study of patients with heart failure, NSAID use increased the risk of MI, hospitalization for heart failure, and death.

Additionally, fluid retention and edema have been observed in some patients treated with NSAIDs. Use of diclofenac may blunt the CV effects of several therapeutic agents used to treat these medical conditions (e.g., diuretics, ACE inhibitors, or angiotensin receptor blockers [ARBs]) [see Drug Interactions (7)] .

Avoid the use of LICART in patients with severe heart failure unless the benefits are expected to outweigh the risk of worsening heart failure. If LICART is used in patients with severe heart failure, monitor patients for signs of worsening heart failure.

5.6 Renal Toxicity and Hyperkalemia

Renal Toxicity

Long-term administration of NSAIDs has resulted in renal papillary necrosis and other renal injury.

Renal toxicity has also been seen in patients in whom renal prostaglandins have a compensatory role in the maintenance of renal perfusion. In these patients, administration of an NSAID may cause a dose-dependent reduction in prostaglandin formation and, secondarily, in renal blood flow, which may precipitate overt renal decompensation. Patients at greatest risk of this reaction are those with impaired renal function, dehydration, hypovolemia, heart failure, liver dysfunction, those taking diuretics and ACE inhibitors or ARBs, and the elderly. Discontinuation of NSAID therapy is usually followed by recovery to the pretreatment state.

No information is available from controlled clinical studies regarding the use of LICART in patients with advanced renal disease. The renal effects of LICART may hasten the progression of renal dysfunction in patients with pre-existing renal disease.

Correct volume status in dehydrated or hypovolemic patients prior to initiating LICART. Monitor renal function in patients with renal or hepatic impairment, heart failure, dehydration, or hypovolemia during use of LICART [see Drug Interactions (7)]. Avoid the use of LICART in patients with advanced renal disease unless the benefits are expected to outweigh the risk of worsening renal function. If LICART is used in patients with advanced renal disease, monitor patients for signs of worsening renal function.

Hyperkalemia

Increases in serum potassium concentration, including hyperkalemia, have been reported with use of NSAIDs, even in some patients without renal impairment. In patients with normal renal function, these effects have been attributed to a hyporeninemic-hypoaldosteronism state.

5.7 Anaphylactic Reactions

Diclofenac has been associated with anaphylactic reactions in patients with and without known hypersensitivity to diclofenac and in patients with aspirin-sensitive asthma [see Contraindications (4) and Warnings and Precautions (5.8)].

Seek emergency help if an anaphylactic reaction occurs.

5.8 Exacerbation of Asthma Related to Aspirin Sensitivity

A subpopulation of patients with asthma may have aspirin-sensitive asthma, which may include chronic rhinosinusitis complicated by nasal polyps; severe, potentially fatal bronchospasm; and/or intolerance to aspirin and other NSAIDs. Because cross-reactivity between aspirin and other NSAIDs has been reported in such aspirin-sensitive patients, LICART is contraindicated in patients with this form of aspirin sensitivity [see Contraindications (4)] . When LICART is used in patients with preexisting asthma (without known aspirin sensitivity), monitor patients for changes in the signs and symptoms of asthma.

5.9 Serious Skin Reactions

NSAIDs, including diclofenac, can cause serious skin adverse reactions such as exfoliative dermatitis, Stevens-Johnson Syndrome (SJS), and toxic epidermal necrolysis (TEN), which can be fatal. NSAIDs can also cause fixed drug eruption (FDE). FDE may present as a more severe variant known as generalized bullous fixed drug eruption (GBFDE), which can be life-threatening.These serious events may occur without warning. Inform patients about the signs and symptoms of serious skin reactions, and to discontinue the use of LICART at the first appearance of skin rash or any other sign of hypersensitivity. LICART is contraindicated in patients with previous serious skin reactions to NSAIDs [see Contraindications (4)] .

5.10 Drug Reaction with Eosinophilia and Systemic Symptoms (DRESS)

Drug Reaction with Eosinophilia and Systemic Symptoms (DRESS) has been reported in patients taking NSAIDs such as LICART. Some of these events have been fatal or life-threatening. DRESS typically, although not exclusively, presents with fever, rash, lymphadenopathy, and/or facial swelling. Other clinical manifestations may include hepatitis, nephritis, hematological abnormalities, myocarditis, or myositis. Sometimes symptoms of DRESS may resemble an acute viral infection. Eosinophilia is often present. Because this disorder is variable in its presentation, other organ systems not noted here may be involved. It is important to note that early manifestations of hypersensitivity, such as fever or lymphadenopathy, may be present even though rash is not evident. If such signs or symptoms are present, discontinue LICART and evaluate the patient immediately .

5.11 Fetal Toxicity

Premature Closure of Fetal Ductus Arteriosus

Avoid use of NSAIDs, including LICART, in pregnant women at about 30 weeks gestation and later. NSAIDs, including LICART, increase the risk of premature closure of the fetal ductus arteriosus at approximately this gestational age.

Oligohydramnios/Neonatal Renal Impairment

Use of NSAIDs, including LICART, at about 20 weeks gestation or later in pregnancy may cause fetal renal dysfunction leading to oligohydramnios and, in some cases, neonatal renal impairment. These adverse outcomes are seen, on average, after days to weeks of treatment, although oligohydramnios has been infrequently reported as soon as 48 hours after NSAID initiation.

Oligohydramnios is often, but not always, reversible with treatment discontinuation. Complications of prolonged oligohydramnios may, for example, include limb contractures and delayed lung maturation. In some postmarketing cases of impaired neonatal renal function, invasive procedures such as exchange transfusion or dialysis were required.

If NSAID treatment is necessary between about 20 weeks and 30 weeks gestation, limit LICART use to the lowest effective dose and shortest duration possible. Consider ultrasound monitoring of amniotic fluid if LICART treatment extends beyond 48 hours. Discontinue LICART if oligohydramnios occurs and follow up according to clinical practice [see Use in Specific Populations (8.1)].

5.12 Hematologic Toxicity

Anemia has occurred in NSAID-treated patients. This may be due to occult or gross blood loss, fluid retention, or an incompletely described effect on erythropoiesis. If a patient treated with LICART has any signs or symptoms of anemia, monitor hemoglobin or hematocrit.

NSAIDs, including LICART, may increase the risk of bleeding events. Co-morbid conditions such as coagulation disorders, concomitant use of warfarin, other anticoagulants, antiplatelet agents (e.g., aspirin), serotonin reuptake inhibitors (SSRIs) and serotonin norepinephrine reuptake inhibitors (SNRIs) may increase this risk. Monitor these patients for signs of bleeding [see Drug Interactions (7)] .

5.13 Masking of Inflammation and Fever

The pharmacological activity of LICART in reducing inflammation, and possibly fever, may diminish the utility of these diagnostic signs in detecting infections.

5.14 Laboratory Monitoring

Because serious GI bleeding, hepatotoxicity, and renal injury can occur without warning symptoms or signs, consider monitoring patients on long-term NSAID treatment with a CBC and a chemistry profile periodically [see Warnings and Precautions (5.2, 5.3, 5.6)] .

5.15 Accidental Exposure in Children

Even a used LICART contains a large amount of diclofenac epolamine (as much as 170 mg). The potential therefore exists for a small child or pet to suffer serious adverse effects from chewing or ingesting a new or used LICART. It is important for patients to store and dispose of LICART out of the reach of children and pets.

5.16 Eye Exposure

Avoid contact of LICART with eyes and mucosa. Advise patients that if eye contact occurs, immediately wash out the eye with water or saline and consult a physician if irritation persists for more than an hour.

5.17 Oral Nonsteroidal Anti-inflammatory Drugs

Concomitant use of oral and topical NSAIDs may result in a higher rate of hemorrhage, more frequent abnormal creatinine, urea and hemoglobin. Do not use LICART in combination with an oral NSAID unless the benefit outweighs the risk and periodic laboratory evaluations are conducted.

6 ADVERSE REACTIONS

The following adverse reactions are discussed in greater detail in other sections of the labeling:

- Cardiovascular Thrombotic Events [see Warnings and Precautions (5.1)]
- GI Bleeding, Ulceration and Perforation [see Warnings and Precautions (5.2)]
- Hepatotoxicity [see Warnings and Precautions (5.3)]
- Hypertension [see Warnings and Precautions (5.4)]
- Heart Failure and Edema [see Warnings and Precautions (5.5)]
- Renal Toxicity and Hyperkalemia [see Warnings and Precautions (5.6)]
- Anaphylactic Reactions [see Warnings and Precautions (5.7)]
- Serious Skin Reactions [see Warnings and Precautions (5.9)]
- Hematologic Toxicity [see Warnings and Precautions (5.12)]

6.1 Clinical Trials Experience

Because clinical trials are conducted under widely varying conditions, adverse reaction rates observed in the clinical trials of a drug cannot be directly compared with rates in the clinical trials of another drug and may not reflect the rates observed in practice.

A total of 874 subjects were exposed to one or more doses of LICART in eleven clinical studies, including approximately 500 subjects who were treated with LICART in six controlled multiple-dose trials. Approximately 400 of these were exposed to the once-a-day 24-hour application, for up to one week in 288 subjects and up to two weeks in 121 subjects.

Adverse Reactions Leading to Discontinuation of Treatment

In the controlled trials, none of the patients given LICART discontinued treatment due to an adverse reaction.

Common Adverse Reactions

Localized Reactions

Overall, the most common adverse reactions associated with LICART treatment were application site skin reactions. Table 1 lists all adverse reactions occurring in ≥ 1% of patients in nine studies (excluding the two dermatologic safety studies) of LICART. A majority of patients treated with LICART experienced adverse reactions with a maximum intensity of "mild" or "moderate".

Table 1. Common Adverse Reactions (by System Organ Class) in ≥ 1% of Patients Treated with LICART or Placebo [The placebo was comprised of the same ingredients as LICART except for diclofenac and may inform adverse reactions associated with the non-active ingredients contained in LICART.] based on Data Pooled from Single-Dose and Multiple-Dose Studies
 | LICART N=573 |  | Placebo N=492
 | N | Percent | N | Percent
General Disorders and Administration Site Conditions | 8 | 1.4 | 19 | 3.9
Application Site Pruritus | 5 | 0.9 | 11 | 2.2
Other Application Site Reactions [Includes application site irritation (6 subjects), application site erythema (3 subjects), application site reaction (4 subjects), application site rash (1 subject), application site inflammation (1 subject), blister (1 subject).] | 5 | 0.9 | 11 | 2.2

6.2 Post-Marketing Experience

The following adverse reactions have been identified during post-approval use of diclofenac topical system. Because these reactions are reported voluntarily from a population of uncertain size, it is not always possible to reliably estimate their frequency or establish a causal relationship to drug exposure.

LICART

Cases suggesting dermal allergic reactions and photoallergic reactions have been reported through foreign post-marketing surveillance.

Diclofenac

Skin and Appendages: Exfoliative dermatitis, Stevens-Johnson Syndrome (SJS), toxic epidermal necrolysis (TEN), fixed drug eruption (FDE) [see Warnings and Precautions (5.9)]

7 DRUG INTERACTIONS

See Table 2 for clinically significant drug interactions with diclofenac.

Table 2: Clinically Significant Drug Interactions with Diclofenac
Drugs That Interfere with Hemostasis
Clinical Impact: | - Diclofenac and anticoagulants such as warfarin have a synergistic effect on bleeding. The concomitant use of diclofenac and anticoagulants have an increased risk of serious bleeding compared to the use of either drug alone. - Serotonin release by platelets plays an important role in hemostasis. Case-control and cohort epidemiological studies showed that concomitant use of drugs that interfere with serotonin reuptake and an NSAID may potentiate the risk of bleeding more than an NSAID alone.
Intervention: | Monitor patients with concomitant use of LICART with anticoagulants (e.g., warfarin), antiplatelet agents (e.g., aspirin), selective serotonin reuptake inhibitors (SSRIs), and serotonin norepinephrine reuptake inhibitors (SNRIs) for signs of bleeding [see Warnings and Precautions (5.12)].
Aspirin
Clinical Impact: | Controlled clinical studies showed that the concomitant use of NSAIDs and analgesic doses of aspirin does not produce any greater therapeutic effect than the use of NSAIDs alone. In a clinical study, the concomitant use of an NSAID and aspirin was associated with a significantly increased incidence of GI adverse reactions as compared to use of the NSAID alone [see Warnings and Precautions (5.2)] .
Intervention: | Concomitant use of LICART and analgesic doses of aspirin is not generally recommended because of the increased risk of bleeding [see Warnings and Precautions (5.12)] .
Intervention: | LICART is not a substitute for low dose aspirin for cardiovascular protection.
ACE Inhibitors, Angiotensin Receptor Blockers, and Beta-Blockers
Clinical Impact: | - NSAIDs may diminish the antihypertensive effect of angiotensin converting enzyme (ACE) inhibitors, angiotensin receptor blockers (ARBs), or beta-blockers (including propranolol).
Clinical Impact: | In patients who are elderly, volume-depleted (including those on diuretic therapy), or have renal impairment, co-administration of an NSAID with ACE inhibitors or ARBs may result in deterioration of renal function, including possible acute renal failure. These effects are usually reversible.
Intervention: | - During concomitant use of LICART and ACE-inhibitors, ARBs, or betablockers, monitor blood pressure to ensure that the desired blood pressure is obtained. - During concomitant use of LICART and ACE-inhibitors or ARBs in patients who are elderly, volume-depleted, or have impaired renal function, monitor for signs of worsening renal function [ see Warnings and Precautions (5.6)] .
Intervention: | When these drugs are administered concomitantly, patients should be adequately hydrated. Assess renal function at the beginning of the concomitant treatment and periodically thereafter.
Diuretics
Clinical Impact: | Clinical studies, as well as post-marketing observations, showed that NSAIDs reduced the natriuretic effect of loop diuretics (e.g., furosemide) and thiazide diuretics in some patients. This effect has been attributed to the NSAID inhibition of renal prostaglandin synthesis.
Intervention: | During concomitant use of LICART with diuretics, observe patients for signs of worsening renal function, in addition to assuring diuretic efficacy including antihypertensive effects [see Warnings and Precautions (5.6)] .
Digoxin
Clinical Impact: | The concomitant use of diclofenac with digoxin has been reported to increase the serum concentration and prolong the half-life of digoxin.
Intervention: | During concomitant use of LICART and digoxin, monitor serum digoxin levels.
Lithium
Clinical Impact: | NSAIDs have produced elevations in plasma lithium levels and reductions in renal lithium clearance . The mean minimum lithium concentration increased 15%, and the renal clearance decreased by approximately 20%. This effect has been attributed to NSAID inhibition of renal prostaglandin synthesis.
Intervention: | During concomitant use of LICART and lithium, monitor patients for signs of lithium toxicity.
Methotrexate
Clinical Impact: | Concomitant use of NSAIDs and methotrexate may increase the risk for methotrexate toxicity (e.g., neutropenia, thrombocytopenia, renal dysfunction).
Intervention: | During concomitant use of LICART and methotrexate, monitor patients for methotrexate toxicity.
Cyclosporine
Clinical Impact: | Concomitant use of LICART and cyclosporine may increase cyclosporine's nephrotoxicity.
Intervention: | During concomitant use of LICART and cyclosporine, monitor patients for signs of worsening renal function.
NSAIDs and Salicylates
Clinical Impact: | Concomitant use of diclofenac with other NSAIDs or salicylates (e.g., diflunisal, salsalate) increases the risk of GI toxicity, with little or no increase in efficacy [see Warnings and Precautions (5.2)].
Intervention: | The concomitant use of diclofenac with other NSAIDs or salicylates is not recommended.
Pemetrexed
Clinical Impact: | Concomitant use of LICART and pemetrexed may increase the risk of pemetrexed-associated myelosuppression, renal, and GI toxicity (see the pemetrexed prescribing information).
Intervention: | During concomitant use of LICART and pemetrexed, in patients with renal impairment whose creatinine clearance ranges from 45 to 79 mL/min, monitor for myelosuppression, renal and GI toxicity.
Intervention: | NSAIDs with short elimination half-lives (e.g., diclofenac, indomethacin) should be avoided for a period of two days before, the day of, and two days following administration of pemetrexed.
Intervention: | In the absence of data regarding potential interaction between pemetrexed and NSAIDs with longer half-lives (e.g., meloxicam, nabumetone), patients taking these NSAIDs should interrupt dosing for at least five days before, the day of, and two days following pemetrexed administration.

8 USE IN SPECIFIC POPULATIONS

8.1 Pregnancy

Risk Summary

Use of NSAIDs, including LICART, can cause premature closure of the fetal ductus arteriosus and fetal renal dysfunction leading to oligohydramnios and, in some cases, neonatal renal impairment. Because of these risks, limit dose and duration of LICART use between about 20 and 30 weeks of gestation, and avoid LICART use at about 30 weeks of gestation and later in pregnancy (see Clinical Considerations and Data).

Premature Closure of Fetal Ductus Arteriosus

Use of NSAIDs, including LICART, at about 30 weeks gestation or later in pregnancy increases the risk of premature closure of the fetal ductus arteriosus.

Oligohydramnios/Neonatal Renal Impairment

Use of NSAIDs at about 20 weeks gestation or later in pregnancy has been associated with cases of fetal renal dysfunction leading to oligohydramnios, and in some cases, neonatal renal impairment.

Data from observational studies regarding other potential embryofetal risks of NSAID use in women in the first or second trimesters of pregnancy are inconclusive.

In animal reproduction studies, diclofenac epolamine administered orally to pregnant rats and rabbits during the period of organogenesis produced embryotoxicity at approximately 3 and 7 times, respectively, the topical exposure from the maximum recommended human dose (MRHD) of LICART. In rats, increased incidences of skeletal anomalies and maternal toxicity were also observed at this dose. Diclofenac epolamine administered orally to both male and female rats prior to mating and throughout the mating period, and during gestation and lactation in females produced embryotoxicity at doses approximately 3 and 7 times, respectively, the topical exposure from the MRHD (see Data) .

Based on animal data, prostaglandins have been shown to have an important role in endometrial vascular permeability, blastocyst implantation, and decidualization. In animal studies, administration of prostaglandin synthesis inhibitors such as diclofenac, resulted in increased pre- and post-implantation loss. Prostaglandins also have been shown to have an important role in fetal kidney development. In published animal studies, prostaglandin synthesis inhibitors have been reported to impair kidney development when administered at clinically relevant doses.

The estimated background risk of major birth defects and miscarriage for the indicated population(s) is unknown. All pregnancies have a background risk of birth defect, loss, or other adverse outcomes. In the U.S. general population, the estimated background risk of major birth defects and miscarriage in clinically recognized pregnancies is 2% to 4% and 15% to 20%, respectively.

Clinical Considerations

Fetal/Neonatal Adverse Reactions

Premature Closure of Fetal Ductus Arteriosus:

Avoid use of NSAIDs in women at about 30 weeks gestation and later in pregnancy, because NSAIDs, including LICART, can cause premature closure of the fetal ductus arteriosus (see Data).

Oligohydramnios/Neonatal Renal Impairment

If an NSAID is necessary at about 20 weeks gestation or later in pregnancy, limit the use to the lowest effective dose and shortest duration possible. If LICART treatment extends beyond 48 hours, consider monitoring with ultrasound for oligohydramnios. If oligohydramnios occurs, discontinue LICART and follow up according to clinical practice (see Data).

Data

Human Data

Premature Closure of Fetal Ductus Arteriosus:

Published literature reports that the use of NSAIDs at about 30 weeks of gestation and later in pregnancy may cause premature closure of the fetal ductus arteriosus.

Oligohydramnios/Neonatal Renal Impairment:

Published studies and postmarketing reports describe maternal NSAID use at about 20 weeks gestation or later in pregnancy associated with fetal renal dysfunction leading to oligohydramnios, and in some cases, neonatal renal impairment. These adverse outcomes are seen, on average, after days to weeks of treatment, although oligohydramnios has been infrequently reported as soon as 48 hours after NSAID initiation. In many cases, but not all, the decrease in amniotic fluid was transient and reversible with cessation of the drug. There have been a limited number of case reports of maternal NSAID use and neonatal renal dysfunction without oligohydramnios, some of which were irreversible. Some cases of neonatal renal dysfunction required treatment with invasive procedures, such as exchange transfusion or dialysis.

Methodological limitations of these postmarketing studies and reports include lack of a control group; limited information regarding dose, duration, and timing of drug exposure; and concomitant use of other medications. These limitations preclude establishing a reliable estimate of the risk of adverse fetal and neonatal outcomes with maternal NSAID use. Because the published safety data on neonatal outcomes involved mostly preterm infants, the generalizability of certain reported risks to the full-term infant exposed to NSAIDs through maternal use is uncertain.

Animal Data

Pregnant Sprague Dawley rats were administered 1, 3, or 6 mg/kg diclofenac epolamine via oral gavage daily from gestation days 6 to15. Maternal toxicity, embryotoxicity, and increased incidence of skeletal anomalies were noted with 6 mg/kg/day diclofenac epolamine, which corresponds to 3-times the maximum recommended daily exposure in humans based on a body surface area comparison. Pregnant New Zealand White rabbits were administered 1, 3, or 6 mg/kg diclofenac epolamine via oral gavage daily from gestation days 6 to18. No maternal toxicity was noted; however, embryotoxicity was evident at 6 mg/kg/day group which corresponds to 7-times the maximum recommended daily exposure in humans based on a body surface area comparison.

Male rats were orally administered diclofenac epolamine (1, 3, 6 mg/kg) for 60 days prior to mating and throughout the mating period, and females were given the same doses 14 days prior to mating and through mating, gestation, and lactation. Embryotoxicity was observed at 6 mg/kg diclofenac epolamine (3-times the maximum recommended daily exposure in humans based on a body surface area comparison), and was manifested as an increase in early resorptions, post-implantation losses, and a decrease in live fetuses. The number of live born and total born were also reduced as was F1 postnatal survival, but the physical and behavioral development of surviving F1 pups in all groups was the same as the deionized water control, nor was reproductive performance adversely affected despite a slight treatment-related reduction in body weight.

8.2 Lactation

Risk Summary

Data from published literature reports with oral preparations of diclofenac indicate the presence of small amounts of diclofenac in human milk (see Data). There are no data on the effects on the breastfed infant or the effects on milk production. The developmental and health benefits of breastfeeding should be considered along with the mother's clinical need for LICART and any potential adverse effects on the breastfed infant from LICART or from the underlying maternal condition.

Data

One woman treated orally with a diclofenac salt, 150 mg/day, had a milk diclofenac level of 100 mcg/L, equivalent to an infant dose of about 0.03 mg/kg/day. Diclofenac was not detectable in breast milk in 12 women using diclofenac (after either 100 mg/day orally for 7 days or a single 50 mg intramuscular dose administered in the immediate postpartum period). The relative bioavailability for LICART is < 1% of a single 50 mg diclofenac tablet.

8.3 Females and Males of Reproductive Potential

Infertility

Females

Based on the mechanism of action, the use of prostaglandin-mediated NSAIDs, including LICART may delay or prevent rupture of ovarian follicles, which has been associated with reversible infertility in some women [see Clinical Pharmacology (12.1)]. Published animal studies have shown that administration of prostaglandin synthesis inhibitors has the potential to disrupt prostaglandin- mediated follicular rupture required for ovulation. Small studies in women treated with NSAIDs have also shown a reversible delay in ovulation. Consider withdrawal of NSAIDs, including LICART, in women who have difficulties conceiving or who are undergoing investigation of infertility.

8.4 Pediatric Use

The safety and effectiveness of LICART in pediatric patients have not been established.

8.5 Geriatric Use

Elderly patients, compared to younger patients, are at greater risk for NSAID-associated serious cardiovascular, gastrointestinal, and/or renal adverse reactions. If the anticipated benefit for the elderly patient outweighs these potential risks, start dosing at the low end of the dosing range, and monitor patients for adverse effects [see Warnings and Precautions (5.1, 5.2, 5.3, 5.6, 5.14)].

Clinical studies of LICART did not include sufficient numbers of subjects aged 65 and over to determine whether they respond differently from younger subjects. Other reported clinical experience has not identified differences in responses between the elderly and younger patients.

10 OVERDOSAGE

Symptoms following acute NSAID overdosages have been typically limited to lethargy, drowsiness, nausea, vomiting, and epigastric pain, which have been generally reversible with supportive care. Gastrointestinal bleeding has occurred. Hypertension, acute renal failure, respiratory depression, and coma have occurred, but were rare [see Warnings and Precautions (5.1, 5.2, 5.4, 5.6)] .

Manage patients with symptomatic and supportive care following an NSAID overdosage. There are no specific antidotes. Forced diuresis, alkalinization of urine, hemodialysis, or hemoperfusion may not be useful due to high protein binding.

For additional information about overdosage treatment, call a poison control center (1-800-222-1222).

11 DESCRIPTION

LICART (diclofenac epolamine) topical system 1.3% is a nonsteroidal anti-inflammatory drug, available for topical application. LICART is a 10 cm × 14 cm topical system comprised of an adhesive material containing 1.3% diclofenac epolamine which is applied to a non-woven polyester felt backing and covered with a polypropylene film release liner. The release liner is removed prior to topical application to the skin.

The chemical name of diclofenac epolamine is 2-[(2,6-dichlorophenyl) amino] benzeneacetic acid, (2-(pyrrolidin-1-yl) ethanol salt, with a molecular formula of C20H24Cl2N2O3 and molecular weight 411.3, an n-octanol/water partition coefficient of 8 at pH 8.5, and the following chemical structure:

Each LICART contains 182 mg of diclofenac epolamine in an aqueous base. Each gram of adhesive contains 13 mg of diclofenac epolamine (equivalent to 9.4 mg diclofenac). Each LICART also contains the following inactive ingredients: butylene glycol, carboxymethylcellulose sodium, dihydroxyaluminum aminoacetate, edetate disodium, gelatin, heparin sodium, kaolin, methylparaben, polysorbate 80, povidone, propylene glycol, propylparaben, sodium polyacrylate, sorbitol solution, tartaric acid, titanium dioxide, and purified water.

12 CLINICAL PHARMACOLOGY

12.1 Mechanism of Action

Diclofenac has analgesic, anti-inflammatory, and antipyretic properties.

The mechanism of action of diclofenac, like that of other NSAIDs, is not completely understood but involves inhibition of cyclooxygenase (COX-1 and COX-2).

Diclofenac is a potent inhibitor of prostaglandin synthesis in vitro. Diclofenac concentrations reached during therapy have produced in vivo effects. Prostaglandins sensitize afferent nerves and potentiate the action of bradykinin in inducing pain in animal models. Prostaglandins are mediators of inflammation. Because diclofenac is an inhibitor of prostaglandin synthesis, its mode of action may be due to a decrease of prostaglandins in peripheral tissues.

Heparin sodium is included in the LICART formulation as an inactive ingredient. In one study in healthy human volunteers activated partial thromboplastin time (aPTT), a measure of coagulation, was unchanged following multiple LICART applications.

12.2 Pharmacodynamics

LICART applied to intact skin provides local analgesia by releasing diclofenac epolamine from the topical system into the skin.

12.3 Pharmacokinetics

Absorption

Following application of LICART once-a-day (24-hour application) for four consecutive days on the front part of the thigh, peak plasma concentrations of diclofenac (range 0.4 – 2.9 ng/mL) were noted between 4 – 20 hours of application, with mean plasma concentrations of diclofenac in the range of 0.5 – 0.9 ng/mL during the application period. On average, after 24 hours of application (medial aspect of the upper arm), about 7 mg of diclofenac are released from the topical system.

Systemic exposure (AUC) and maximum plasma concentrations of diclofenac, after repeated dosing for four days with LICART were lower (<1%) than after a single oral 50-mg diclofenac sodium tablet.

The pharmacokinetics of LICART have been evaluated in healthy volunteers (1) at rest (i.e., under normal behavior), (2) undergoing moderate exercise (three cycling sessions of 20 minutes each, at 50% of Heart Rate Reserve above heart rate at rest, performed at several minutes and 4 and 8 hours after topical system application), (3) under occlusion (elastic occlusive bandage over the entire topical system during 24 hours of application, except two 1-hour periods of non-occlusion, 5 and 12 hours after topical system application), and (4) exposed to moderate heat (immediately after topical system application and 4, 8 and 12 hours thereafter over four consecutive days, warmed with a heat wrap for 20 minutes, with total heat exposure of 5 hours and 20 minutes). Moderate exercise, occlusion and moderate heat all increased (~ 20%) the peak plasma concentration (Cmax) and the systemic exposure (AUC) of diclofenac (see Table 3).

Table 3: Diclofenac pharmacokinetics behavior following various LICART application modalities
Parameter | Normal | Moderate Exercise | Under Occlusion | Moderate Heat
Cmax (ng/mL) | 1.01±0.64 | 1.22±0.76 | 1.14±0.74 | 1.23±0.73
Tmax (h) | 6 (4–20) | 12 (0-24) | 6 (0-24) | 6 (0-20)
AUCτ (ng/mL×h) | 18.58±11.63 | 22.77±14.39 | 21.94±14.25 | 23.07±14.29
Cmin (ng/mL) | 0.49±0.31 | 0.62±0.42 | 0.63±0.47 | 0.69±0.46
Values are arithmetic means ± SD, except for Tmax: median (min - max).

Distribution

Diclofenac has a very high affinity (>99%) for human serum albumin. Diclofenac diffuses into and out of the synovial fluid. Diffusion into the joint occurs when plasma levels are higher than those in the synovial fluid, after which the process reverses and synovial fluid levels are higher than plasma levels. It is not known whether diffusion into the joint plays a role in the effectiveness of diclofenac.

Elimination

Metabolism

Five diclofenac metabolites have been identified in human plasma and urine. The metabolites include 4'-hydroxy-, 5-hydroxy-, 3'-hydroxy-, 4',5-dihydroxy- and 3'-hydroxy-4'-methoxy diclofenac. The major diclofenac metabolite, 4'-hydroxy-diclofenac, has very weak pharmacologic activity. The formation of 4'-hydroxy- diclofenac is primarily mediated by CPY2C9. Both diclofenac and its oxidative metabolites undergo glucuronidation or sulfation followed by biliary excretion. Acylglucuronidation mediated by UGT2B7 and oxidation mediated by CPY2C8 may also play a role in diclofenac metabolism. CYP3A4 is responsible for the formation of minor metabolites, 5-hydroxy and 3'-hydroxy- diclofenac.

Excretion

The plasma elimination half-life of diclofenac after application of LICART is approximately 12 hours. Diclofenac is eliminated through metabolism and subsequent urinary and biliary excretion of the glucuronide and the sulfate conjugates of the metabolites. Little or no free unchanged diclofenac is excreted in the urine. Approximately 65% of the dose is excreted in the urine and approximately 35% in the bile as conjugates of unchanged diclofenac plus metabolites.

Specific Populations

The pharmacokinetics of LICART has not been investigated in children, patients with hepatic or renal impairment, or specific racial groups.

Drug Interaction Studies

Aspirin: When NSAIDs were administered with aspirin, the protein binding of NSAIDs was reduced, although the clearance of free NSAID was not altered. The clinical significance of this interaction is not known. See Table 2 for clinically significant drug interactions of NSAIDs with aspirin [see Drug Interactions (7)].

13 NONCLINICAL TOXICOLOGY

13.1 Carcinogenesis, Mutagenesis, Impairment of Fertility

Carcinogenesis

Long-term studies in animals have not been performed to evaluate the carcinogenic potential of either diclofenac epolamine or LICART.

Mutagenesis

Diclofenac epolamine is not mutagenic in Salmonella typhimurium strains, nor does it induce an increase in metabolic aberrations in cultured human lymphocytes, or the frequency of micronucleated cells in the bone marrow micronucleus test performed in rats.

Impairment of Fertility

Male and female Sprague Dawley rats were administered 1, 3, or 6 mg/kg/day diclofenac epolamine via oral gavage (males treated for 60 days prior to conception and during mating period, females treated for 14 days prior to mating through day 19 of gestation). Diclofenac epolamine treatment with 6 mg/kg/day resulted in increased early resorptions and post-implantation losses; however, no effects on the mating and fertility indices were found. The 6 mg/kg/day dose corresponds to 3 times the maximum recommended daily exposure in humans based on a body surface area comparison.

14 CLINICAL STUDIES

14.1 Minor Soft Tissue Injuries (Sprain, Contusion)

The efficacy of LICART was demonstrated in two randomized, double-blind, parallel-arm, placebo- and active-controlled studies in patients with minor sprains, strains, and/or contusions. Patients were randomized equally to receive LICART, placebo, or FLECTOR and treatment was applied as a 24-hour, once daily application for 7 or 14 days. FLECTOR was not administered according to its approved twice daily (BID) dosing regimen; therefore, conclusions regarding comparative efficacy between LICART and FLECTOR cannot be made based on these studies.

One study enrolled 429 adult patients aged 18 to 65 years with ankle sprain who had a mean baseline pain intensity on movement of 72 mm on a 0-100 mm visual analog scale (VAS). The second study enrolled 355 adult patients aged 18-75 years with muscle contusion of the limb who had a mean baseline pain on movement intensity of 68 mm on a 0-100 mm VAS. The primary efficacy endpoint was the mean change from baseline in pain on movement to Day 3 of treatment, where pain on movement was assessed twice daily (i.e., morning and evening) for 7 days in the ankle sprain study (06EU/FHp03) and 14 days in the muscle contusion study (05DCz/FHp11). In both studies, LICART demonstrated a statistically significant difference versus placebo on the primary efficacy endpoint, reduction in pain on movement at Day 3.

Figure 1: Pain on movement intensity score differences from baseline in the muscle contusion study (Protocol 05DCz/FHp11).

Figure 2: Pain on movement intensity score differences from baseline in the ankle sprain study (Protocol 06EU/FHp03).

Based on a clinical study in 28 subjects with LICART applied to the lower leg above the ankle, 28 subjects (100%) had adhesion scores of 0 (≥90% adhered) for all evaluations performed every 4 hours during the 24-hour wear period.

16 HOW SUPPLIED/STORAGE AND HANDLING

The LICART (diclofenac epolamine) topical system 1.3% is supplied in re-sealable envelopes, each containing 5 topical systems (10 cm × 14 cm EACH) (NDC 71858-0305-4), with 3 envelopes per box (NDC 71858-0305-5). Each LICART is debossed with "LICART (diclofenac epolamine) topical system 1.3%".

- Keep out of reach of children and pets.
- Envelopes should be sealed at all times when not in use.

Storage

Store at 20 °C to 25 °C (68 °F to 77 °F); excursions permitted between 15 °C to 30 °C (59 °F to 86 °F) [see USP Controlled Room Temperature]. Once the envelope has been opened, LICART is stable up to 6 months, if stored at room temperature in the re-sealed envelope.

17 PATIENT COUNSELING INFORMATION

Advise the patient to read the FDA-approved patient labeling (Medication Guide) that accompanies each prescription dispensed, as well as the Directions for Use on the product packaging. Inform patients, families, or their caregivers of the following information before initiating therapy with LICART and periodically during the course of ongoing therapy.

Cardiovascular Thrombotic Events

Advise patients to be alert for the symptoms of cardiovascular thrombotic events, including chest pain, shortness of breath, weakness, or slurring of speech, and to report any of these symptoms to their health care provider immediately [see Warnings and Precautions (5.1)].

Gastrointestinal Bleeding, Ulceration, and Perforation

Advise patients to report symptoms of ulcerations and bleeding, including epigastric pain, dyspepsia, melena, and hematemesis to their health care provider. In the setting of concomitant use of low-dose aspirin for cardiac prophylaxis, inform patients of the increased risk for and the signs and symptoms of GI bleeding [see Warnings and Precautions (5.2)] .

Hepatotoxicity

Inform patients of the warning signs and symptoms of hepatotoxicity (e.g., nausea, fatigue, lethargy, pruritus, diarrhea, jaundice, right upper quadrant tenderness, and "flu-like" symptoms). If these occur, instruct patients to stop LICART and seek immediate medical therapy [see Warnings and Precautions (5.3)] .

Heart Failure and Edema

Advise patients to be alert for the symptoms of congestive heart failure including shortness of breath, unexplained weight gain, or edema and to contact their healthcare provider if such symptoms occur [see Warnings and Precautions (5.5)].

Anaphylactic Reactions

Inform patients of the signs of an anaphylactic reaction (e.g., difficulty breathing, swelling of the face or throat). Instruct patients to seek immediate emergency help if these occur [see Contraindications (4) and Warnings and Precautions (5.7)].

Serious Skin Reactions, including DRESS

Advise patients to stop using LICART immediately if they develop any type of rash or fever and to contact their healthcare provider as soon as possible [see Warnings and Precautions (5.9, 5.10)] .

Female Fertility

Advise females of reproductive potential who desire pregnancy that NSAIDs, including LICART, may delay or prevent rupture of ovarian follicles, which has been associated with a reversible infertility in some women [see Use in Specific Populations (8.3)]

Fetal Toxicity

Inform pregnant women to avoid use of LICART and other NSAIDs starting at 30 weeks' gestation because of the risk of the premature closure of the fetal ductus arteriosus. If treatment with LICART is needed for a pregnant woman between about 20 to 30 weeks gestation, advise her that she may need to be monitored for oligohydramnios, if treatment continues for longer than 48 hours [see Warnings and Precautions (5.11) and Use in Specific Populations (8.1)].

Avoid Concomitant Use of other NSAIDs

Inform patients that the concomitant use of LICART with other NSAIDs or salicylates (e.g., diflunisal, salsalate) is not recommended due to the increased risk of gastrointestinal toxicity, and little or no increase in efficacy [see Warnings and Precautions (5.2) and Drug Interactions (7)] . Alert patients that NSAIDs may be present in "over-the-counter" medications for treatment of colds, fever, or insomnia.

Use of NSAIDs and Low-Dose Aspirin

Inform patients not to use low-dose aspirin concomitantly with LICART until they talk to their healthcare provider [see Drug Interactions (7)] .

Eye Exposure

Instruct patients to avoid contact of LICART with the eyes and mucosa. Advise patients that if eye contact occurs, immediately wash out the eye with water or saline and consult a physician if irritation persists for more than an hour [see Warnings and Precautions (5.15)].

Special Application Instructions

- Instruct patients that, if LICART begins to peel-off, the edges of the topical system may be taped down. If problems with adhesion persist, patients may overlay the topical system with a mesh netting sleeve, where appropriate (e.g., to secure topical systems applied to ankles, knees, or elbows). The mesh netting sleeve (e.g., Curad® Hold Tite™, Surgilast® Tubular Elastic Dressing) must allow air to pass through and not be occlusive (non-breathable) [Curad ® Hold Tite™ is a trademark of Medline Industries, Inc., and Surgilast ® Tubular Elastic Dressing is a trademark of Derma Sciences, Inc.] .
- Instruct patients that LICART may not be applied to non-intact or damaged skin resulting from any etiology, e.g., exudative dermatitis, eczema, infected lesion, burns or wounds.
- Instruct patients not to wear LICART when bathing or showering.
- Instruct patients to avoid contact with eyes.
- Instruct patients to wash hands after applying, handling or removing the topical system.

Manufactured for: IBSA Institut Biochimique SA, 6912 Pazzallo, Switzerland

Distributed by: IBSA Pharma Inc., Parsippany, NJ 07054 USA

Medication Guide for Nonsteroidal Anti-inflammatory Drugs (NSAIDs)

What is the most important information I should know about medicines called Nonsteroidal Anti- inflammatory Drugs (NSAIDs)?

NSAIDs can cause serious side effects, including:

- Increased risk of a heart attack or stroke that can lead to death. This risk may happen early in treatment and may increase:
  - with increasing doses of NSAIDs
  - with longer use of NSAIDs
  Do not take NSAIDs right before or after a heart surgery called a "coronary artery bypass graft (CABG)."
  Avoid taking NSAIDs after a recent heart attack, unless your healthcare provider tells you to. You may have an increased risk of another heart attack if you take NSAIDs after a recent heart attack.
- Increased risk of bleeding, ulcers, and tears (perforation) of the esophagus (tube leading from the mouth to the stomach), stomach and intestines:
  - anytime during use
  - without warning symptoms
  - that may cause death

The risk of getting an ulcer or bleeding increases with:

- past history of stomach ulcers, or stomach or intestinal bleeding with use of NSAIDs
- taking medicines called "corticosteroids", "anticoagulants", "SSRIs", or "SNRIs"
- increasing doses of NSAIDs
- longer use of NSAIDs
- smoking
- drinking alcohol
- older age
- poor health
- advanced liver disease
- bleeding problems

NSAIDs should only be used:

- exactly as prescribed
- at the lowest dose possible for your treatment
- for the shortest time needed

What are NSAIDs?

NSAIDs are used to treat pain and redness, swelling, and heat (inflammation) from medical conditions such as different types of arthritis, menstrual cramps, and other types of short-term pain.

Who should not take NSAIDs?

Do not take NSAIDs:

- if you have had an asthma attack, hives, or other allergic reaction with aspirin or any other NSAIDs.
- right before or after heart bypass surgery.

Before taking NSAIDS, tell your healthcare provider about all of your medical conditions, including if you:

- have liver or kidney problems
- have high blood pressure
- have asthma
- are pregnant or plan to become pregnant. Taking NSAIDs at about 20 weeks of pregnancy or later may harm your unborn baby. If you need to take NSAIDs for more than 2 days when you are between 20 and 30 weeks of pregnancy, your healthcare provider may need to monitor the amount of fluid in your womb around your baby. You should not take NSAIDs after about 30 weeks of pregnancy.
- are breastfeeding or plan to breast feed .

Tell your healthcare provider about all of the medicines you take, including prescription or over-the- counter medicines, vitamins or herbal supplements. NSAIDs and some other medicines can interact with each other and cause serious side effects. Do not start taking any new medicine without talking to your healthcare provider first.

What are the possible side effects of NSAIDs?

NSAIDs can cause serious side effects, including:

See " What is the most important information I should know about medicines called Nonsteroidal Anti- inflammatory Drugs (NSAIDs)?"

- new or worse high blood pressure
- heart failure
- liver problems including liver failure
- kidney problems including kidney failure
- low red blood cells (anemia)
- life-threatening skin reactions
- life-threatening allergic reactions
- Other side effects of NSAIDs include: stomach pain, constipation, diarrhea, gas, heartburn, nausea, vomiting, and dizziness.

Get emergency help right away if you get any of the following symptoms:

- shortness of breath or trouble breathing
- chest pain
- weakness in one part or side of your body

- slurred speech
- swelling of the face or throat

Stop taking your NSAID and call your healthcare provider right away if you get any of the following symptoms:

- nausea
- more tired or weaker than usual
- diarrhea
- itching
- your skin or eyes look yellow
- indigestion or stomach pain
- flu-like symptoms

- vomit blood
- there is blood in your bowel movement or it is black and sticky like tar
- unusual weight gain
- skin rash or blisters with fever
- swelling of the arms, legs, hands and feet

If you take too much of your NSAID, call your healthcare provider or get medical help right away.

These are not all the possible side effects of NSAIDs. For more information, ask your healthcare provider or pharmacist about NSAIDs.

Call your doctor for medical advice about side effects. You may report side effects to FDA at 1-800-FDA-1088.

Other information about NSAIDs

- Aspirin is an NSAID but it does not increase the chance of a heart attack. Aspirin can cause bleeding in the brain, stomach, and intestines. Aspirin can also cause ulcers in the stomach and intestines.
- Some NSAIDs are sold in lower doses without a prescription (over-the counter). Talk to your healthcare provider before using over-the-counter NSAIDs for more than 10 days.

General information about the safe and effective use of NSAIDs

Medicines are sometimes prescribed for purposes other than those listed in a Medication Guide. Do not use NSAIDs for a condition for which it was not prescribed. Do not give NSAIDs to other people, even if they have the same symptoms that you have. It may harm them.

If you would like more information about NSAIDs, talk with your healthcare provider. You can ask your pharmacist or healthcare provider for information about NSAIDs that is written for health professionals.

Manufactured for: IBSA Institut Biochimique SA, 6912 Pazzallo, Switzerland
Distributed by: IBSA Pharma Inc., Parsippany, NJ 07054 USA

For more information, go to www.licart.com or call 1-800-587-3513
This Medication Guide has been approved by the U.S. Food and Drug Administration. Revised: 11/2022

1235 edition V 11.22

PRINCIPAL DISPLAY PANEL - 15 Patch Carton

NDC 71858-0305-5

Licart®
(diclofenac epolamine) topical system 1.3%

CHANGE LICART ONCE DAILY 24hr

Rx Only

15 TOPICAL SYSTEMS (10 CM X 14 CM EACH)

Dispense with enclosed Medication Guide

Fold the used topical systems so that the adhesive side sticks to itself and safely discard used topical systems where children and pets cannot get them

IBSA